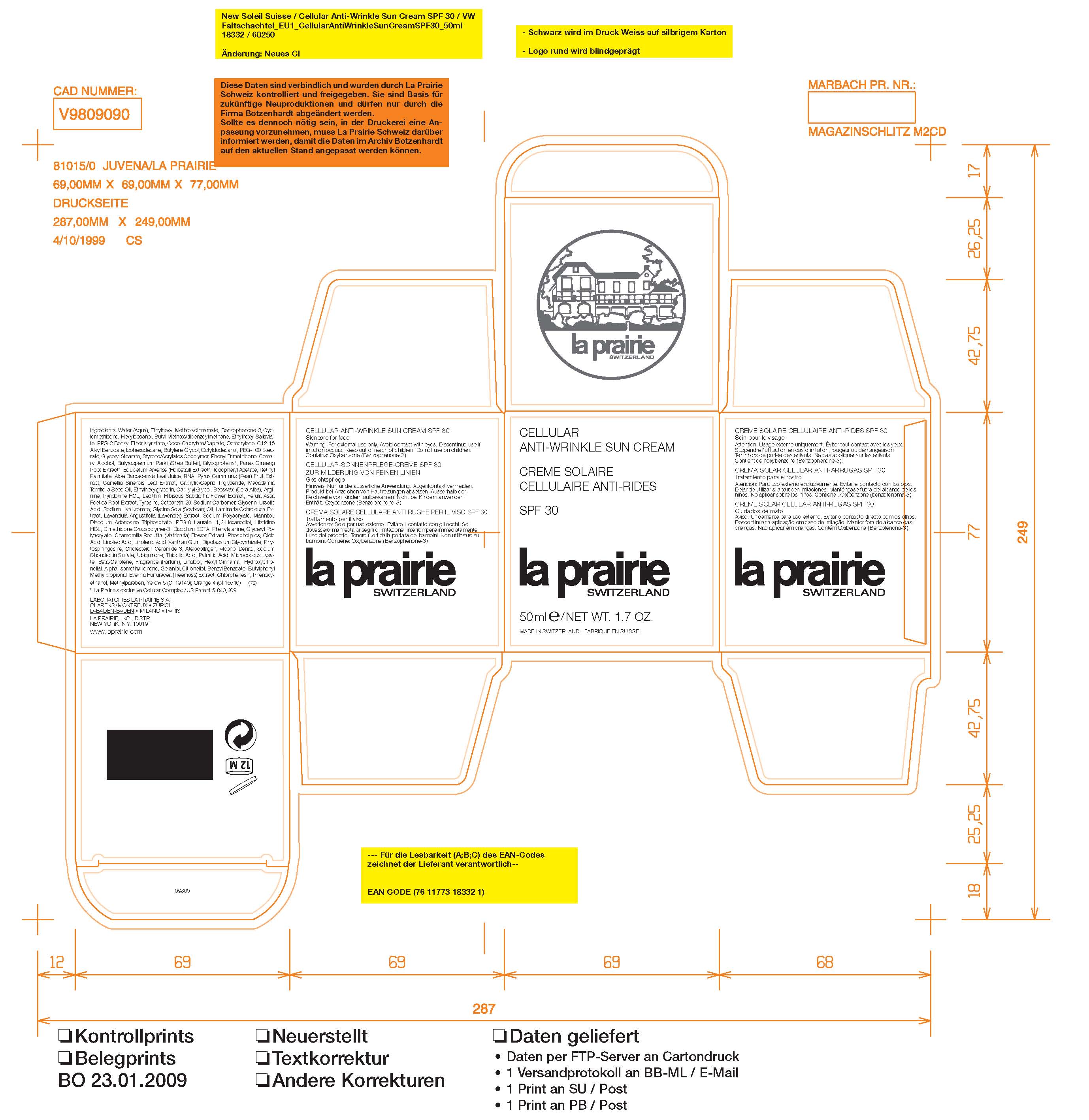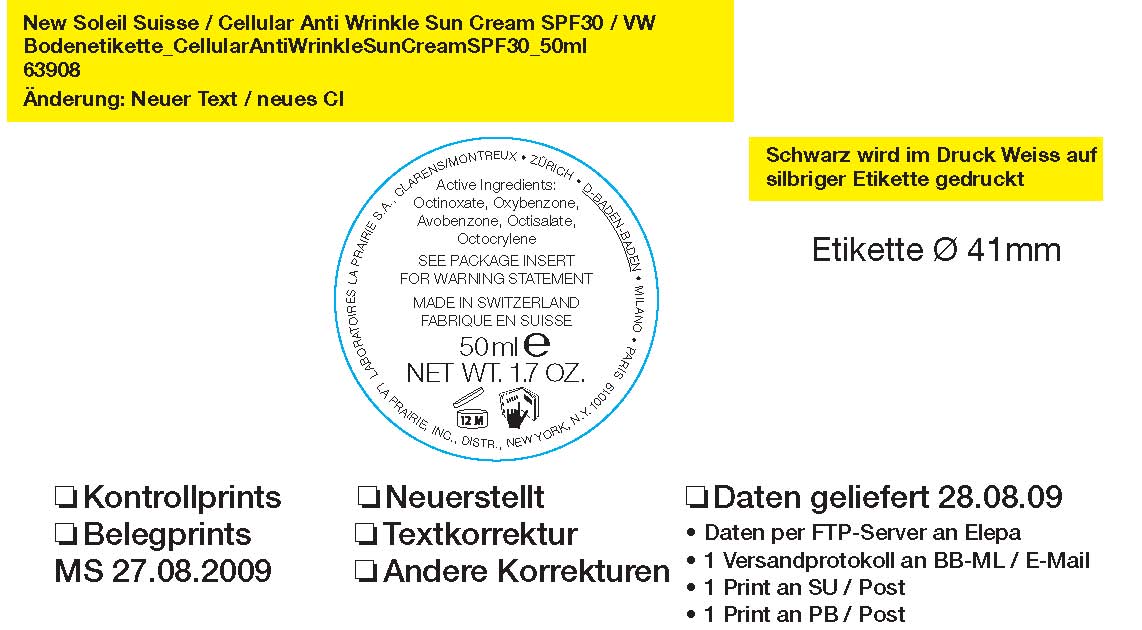 DRUG LABEL: La Prairie Switzerland
NDC: 59614-411 | Form: CREAM
Manufacturer: Juvena Produits de Beaute GMBH
Category: otc | Type: HUMAN OTC DRUG LABEL
Date: 20100601

ACTIVE INGREDIENTS: AVOBENZONE 3 mL/100 mL; OCTINOXATE 7.5 mL/100 mL; OCTISALATE 2.6 mL/100 mL; OCTOCRYLENE 2.4 mL/100 mL; OXYBENZONE 5 mL/100 mL

Cellular Anti-Wrinkle Sun Screen SPF 30

Active Ingredients:
Octinoxate 7.5%
Oxybenzone 5%
Avobenzone 3%
Octisalate 2.6%
Octocrylene 2.4%

WARNINGS

Warnings: For external use only. Avoid contact with eyes. Discontinue use if irritation occurs. Keep out of reach of children. Do not use on children. Contains: Oxybenzone (Benzophenone-3)

INACTIVE INGREDIENT

Ingredients: Water (Aqua), Ethylhexyl Methoxycinnimate, Benzophenone-3, Cyclomethicone, Hexyldecanol, Butylene Methoxydibenzoylmethane, Ethylhexyl Salicylate, PPG-3 Benzyl Ether Myristate, Coco-Caprylate/Caprate, Octocrylene, C12-15 Alkyl Benzoate, Isohexadecane, Butylene Glycol, Octyldodecanol, PEG-100 Stearate, Glyceryl Stearate, Styrene/Actylates Copolymer, Phenyl Trimethicone, Cetearyl Alcohol, Butyrospermum Parkii (Shea Butter), Glycoproteins, Panax Ginseng Root Extract, Equisetum Arvense (Horsetail) Extract, Tocopheryl Acetate, Retinyl Palmitate, Aloe Barbadensis Leaf Juice, RNA, Pyrus Communis (Pear) Fruit Extract, Camellia Sinensis Leaf Extract, Caprylic/Capric Triglyceride, Macadamia Ternifolia Seed Oil, Ethylhexylglycerin, Caprylyl Glycol, Beeswax (Cera Alba), Arginine, Pyridoxine HCL, Lecithin, Hibisus Sabdariffa Flower Extract, Ferula Assa Foetida Root Extract, Tyrosine, Ceteareth-20, Sodium Carbomer, Glycerin, Ursolic Acid, Sodium Hyaluronate, Glycine Soja (soybean) Oil, laminaria Ochroleuca Extract, Lavandula Angustifolia (lavender) extract, sodium polyacrylate, mannitol, disodium adenosine triphosphate, PEG-8 Laurate, 1,2-Hexanediol, histidine HCL, Dimethicone Crosspolymer-3, disodium EDTA, phenylalanine, Glyceryl Polyacrylate, Chamomilla Recutita (Matricaria) Flower Extract, Phospholipids, Oleic Acid, Linoleic Acid, Linolenic Acid, Xanthan Gum, Dipotassium Glycyrrihizate, Phytosphingosine, Cholesterol, Ceramide 3, Atelocollagen, Alcohol Denat., Sodium Chondroitin Sulfate, Ubiquinone, Thiotic Acid, Palmitic Acid, Micrococcus Lysate, Beta-Carotene, Fragrance (Parfum), Linalool, Hexyl Cinnamal, Hydroxycitronellal, Alpha-Isomethl Ionone, Geraniol, Citronellol, Benzyl Benzoate, Butylphenyl Methylpropional, Evernia Furfuracea (Treemoss) Extract, Chlorphenesin, Phenoxyethanol, Methylparaben, Yellow 5 (CI 19140), Orange 4 (CI 15510)

PACKAGE LABEL

La Prairie Switerland

Cellular Anti-Wrinkle Sun Cream SPF 30

50 ml / NET Wt. 1.7oz.